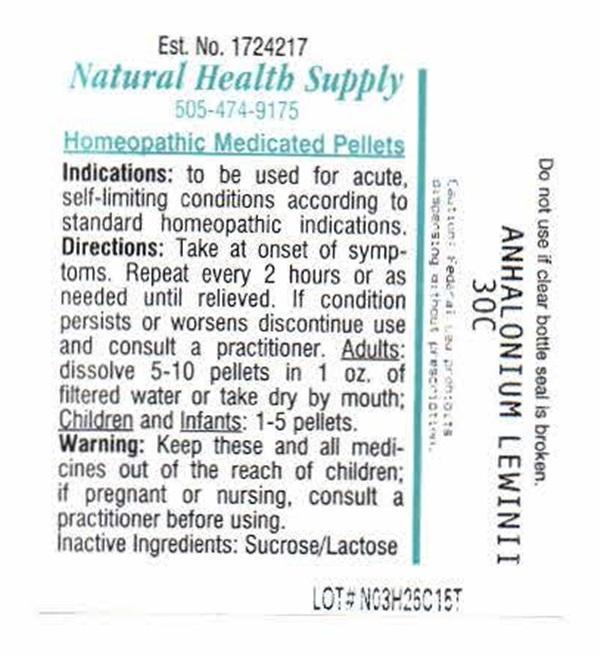 DRUG LABEL: ANNALONIUM LEWINII
NDC: 64117-400 | Form: PELLET
Manufacturer: Natural Health Supply
Category: homeopathic | Type: HUMAN PRESCRIPTION DRUG LABEL
Date: 20210118

ACTIVE INGREDIENTS: LOPHOPHORA WILLIAMSII FLOWER 30 [hp_C]/1 1
INACTIVE INGREDIENTS: SUCROSE; LACTOSE

ANNALONIUM LEWINII

INDICATIONS AND USAGE

Indications: to be used for acute, self-limiting conditions according to standard homeopathic indications.

DOSAGE AND ADMINISTRATION

Directions:Take at onset of symptoms. Repeat every 2 hours of as needed until relieved. If condition persists or worsens discontinue use and consult a practitioner.

Adults: dissolve 5 - 10 pellets in 1 oz. of filtered water or take dry by mouth;

Children and Infants: 1-5 pellets.

WARNINGS

Keep these and all medicines out of the reach of children; if pregnant or nursing, consult a practitioner before using.

Inactive Ingredients:Sucrose, laxctose

PACKAGE LABEL

Est No. 1724217

Natural Health Supply

505-474-9175

Homeopathic Medicate Pellets

Do not use if clear bottle seal is broken.

Caution:Federal Law prohibits dispensing without prescription.

LOT # N03H26C15T